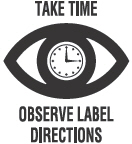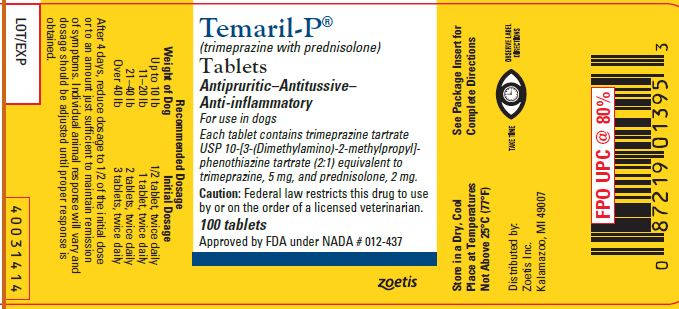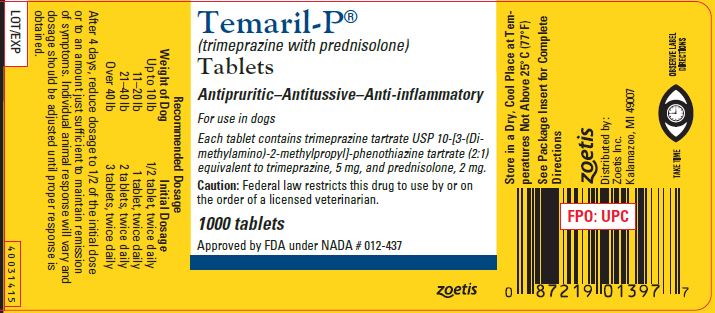 DRUG LABEL: Temaril-P
NDC: 54771-8550 | Form: TABLET
Manufacturer: Zoetis Inc.
Category: animal | Type: PRESCRIPTION ANIMAL DRUG LABEL
Date: 20230112

ACTIVE INGREDIENTS: TRIMEPRAZINE TARTRATE 5 mg/1 1; PREDNISOLONE 2 mg/1 1

Temaril-P®

Temaril-P®
(trimeprazine with prednisolone)
Tablets

Antipruritic–Antitussive–Anti-inflammatory

For use in dogs

CAUTION

Federal law restricts this drug to use by or on the order of a licensed veterinarian.

DESCRIPTION

Each tablet contains trimeprazine tartrate (USP) 10-[3-(Dimethylamino)-2-methylpropyl] phenothiazine tartrate (2:1) equivalent to trimeprazine, 5 mg, and prednisolone, 2 mg.

Action

The exclusive Temaril-P formula combines the antipruritic and antitussive action of trimeprazine with the anti-inflammatory action of prednisolone. A therapeutic effect is attained by administering the tablets twice daily.

INDICATIONS AND USAGE

1. Antipruritic

Temaril-P is recommended for the relief of itching regardless of cause. Its usefulness has been demonstrated for the relief of itching and the reduction of inflammation commonly associated with most skin disorders of dogs such as the eczema caused by internal disorders, otitis, and dermatitis (allergic, parasitic, pustular, and nonspecific). It often relieves pruritus which does not respond to other therapy. With any pruritus treatment, the cause should be determined and corrected; otherwise, signs are likely to recur following discontinuance of therapy.

2. Antitussive

Temaril-P has been found to be effective therapy and adjunctive therapy in various cough conditions of dogs. Therefore, in addition to its antipruritic action, Temaril-P is recommended for the treatment of "kennel cough" or tracheobronchitis, bronchitis including all allergic bronchitis, and infections and coughs of nonspecific origin. (Coughs due to cardiac insufficiencies would not be expected to respond to Temaril-P therapy.) As with any antitussive treatment, the etiology of the cough should be determined and eliminated if possible. Otherwise, symptoms are likely to recur following discontinuance of therapy.

Note: Temaril-P may be administered to animals suffering from acute or chronic bacterial infections provided the infection is controlled by appropriate antibiotic or chemotherapeutic agents.

WARNING

Clinical and experimental data have demonstrated that corticosteroids administered orally or by injection to animals may induce the first stage of parturition if used during the last trimester of pregnancy and may precipitate premature parturition followed by dystocia, fetal death, retained placenta, and metritis. Additionally, corticosteroids administered to dogs, rabbits, and rodents during pregnancy have resulted in cleft palate in offspring. Corticosteroids administered to dogs during pregnancy have also resulted in other congenital anomalies, including deformed forelegs, phocomelia, and anasarca. If a vasoconstrictor is needed, norepinephrine should be used in lieu of epinephrine. Phenothiazine derivatives may reverse the usual elevating action of epinephrine causing a further lowering of blood pressure.

PRECAUTIONS AND SIDE EFFECTS

All the precautions applicable to cortisone and to phenothiazine derivatives apply also to Temaril-P. Possible side effects attributable to corticosteroids include sodium retention and potassium loss, negative nitrogen balance, suppressed adrenal cortical function, delayed wound healing, osteoporosis, elevated levels of SGPT and SAP, and vomiting and diarrhea (occasionally bloody). Cushings syndrome in dogs has been reported in association with prolonged or repeated steroid therapy. Possible increased susceptibility to bacterial invasion and/or the exacerbation of preexisting bacterial infection may occur in patients receiving corticosteroids. As noted above, however, this problem can be avoided by concomitant use of appropriate anti-infective agents. Possible side effects attributable to phenothiazine derivatives include sedation; protruding nictitating membrane; blood dyscrasias; intensification and prolongation of the action of analgesics, sedatives and general anesthetics; and potentiation of organophosphate toxicity and the activity of procaine hydrochloride.

It should be remembered that the premonitory signs of cortisone overdosage, such as sodium retention and edema, may not occur with prednisolone. Therefore, the veterinarians must be alert to detect less obvious side effects, such as blood dyscrasias, polydipsia, and polyuria.

The appearance and severity of side effects are dose related and are minimal at the recommended dosage level. If troublesome side effects are encountered, the dosage of Temaril-P should be reduced and discontinued unless the severity of the condition being treated makes its relief paramount.

Prolonged treatment with Temaril-P must be withdrawn gradually. Use of corticosteroids, depending on dose, duration, and specific steroid, may result in inhibition of endogenous steroid production following drug withdrawal. In patients presently receiving or recently withdrawn from systemic steroid treatments, therapy with a rapidly acting corticosteroid should be considered in unusually stressful situations.

DOSAGE AND ADMINISTRATION

The same dosage schedule may be followed for both antipruritic and antitussive therapy.

Weight of Dog | Initial Dosage
Up to 10 lb | 1/2 tablet, twice daily
11–20 lb | 1 tablet, twice daily
21–40 lb | 2 tablets, twice daily
Over 40 lb | 3 tablets, twice daily

After 4 days, reduce dosage to 1/2 of the initial dose or to an amount just sufficient to maintain remission of symptoms. Individual animal response will vary and dosage should be adjusted until proper response is obtained.

STORAGE AND HANDLING

Store in a Dry, Cool Place at Temperatures Not Above 25°C (77°F)

HOW SUPPLIED

100- and 1000-tablet bottles.

REFERENCES

1. Knowles JO, Knowles RP: Preliminary reports on an effective antipruritic agent. Vet Med 55(8):67–68, 1960.
2. Candlin FT: An agent to aid in control of pruritus. Vet Med 56(5):207–208, 1961.
3. Yoxall AT, Hird JRF: Pharmacological Basis of Small Animal Medicine. Blackwell Scientific Publications, London, pp. 99–102, 1979.
4. Booth N, McDonald LE: Veterinary Pharmacology and Therapeutics, 5th ed. Iowa State University Press, Ames, pp. 564–570, 1982.
5. Davis L: Handbook of Small Animal Therapeutics.Churchill Livingstone, New York, pp. 140–142; 459–461; 468–469, 1985.
6. Scott D: Systemic glucocorticoid therapy. Current Veterinary Therapy, Kirk WV Saunders, ed., Philadelphia, pp. 988–994, 1980.
7. Lecture: “Rational Steroid Therapy” Duncan C. Ferguson, VMD, PhD, Department of Pharmacology, Cornell University.
8. Kemppianen RJ, Lorenz MD, Thompson FN: Adrenocortical suppression in the dog given a single intramuscular dose of prednisolone or triamcinolone acetonide. Am J Vet Res 42(2):204–206, 1982.
9. Rogers WA, Ruebner BH: A retrospective study of probable glucocorticoid induced hepatopathy in dogs. JAVMA 1977;170(6): 603-605.

Approved by FDA under NADA # 012-437

zoetis

Distributed by:

Zoetis Inc.

Kalamazoo, MI 49007

40031413

Revised: May 2020

PRINCIPAL DISPLAY PANEL - 100 Tablet Bottle Label

40031414

PRINCIPAL DISPLAY PANEL - 1000 Tablet Bottle Label

40031415